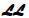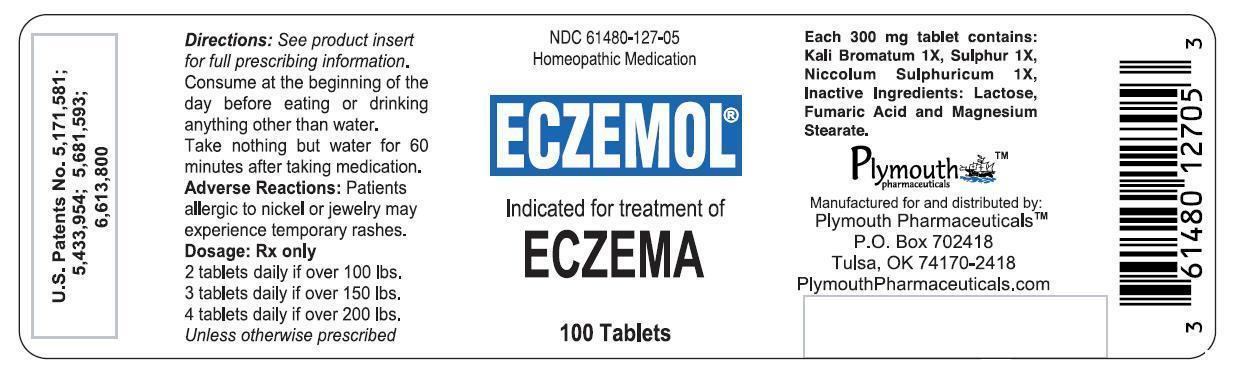 DRUG LABEL: Eczemol
NDC: 61480-127 | Form: TABLET
Manufacturer: PLYMOUTH HEALTHCARE PRODUCTS LLC
Category: homeopathic | Type: HUMAN PRESCRIPTION DRUG LABEL
Date: 20251120

ACTIVE INGREDIENTS: POTASSIUM BROMIDE 1 [hp_X]/1 1; NICKEL SULFATE 1 [hp_X]/1 1; SULFUR 1 [hp_X]/1 1

ECZEMOL®

CAUTION

Federal law prohibits dispensing without a prescription.

DESCRIPTION

ECZEMOL®is a biochemical homeopathic medication indicated for the treatment of eczema.^27,29The active ingredients in each ECZEMOL®tablet consist of the following: Potassium Bromide (Kali Bromatum) 1X, Sulphur 1X, and Nickel Sulphate (Niccolum Sulphuricum) 1X. These drug ingredients are listed in the Homoeopathic Pharmacopoeia of the United States (HPUS).^1

Inactive ingredients: Lactose, Fumaric Acid, and Magnesium Stearate.

Pharmacological class:Homeopathic drug.

Dosage form:Oral 300 mg scored tablet. May be swallowed whole, chewed or dissolved in the mouth and swallowed.

CLINICAL PHARMACOLOGY

The active ingredients in ECZEMOL®are simple biochemical compounds. The exact mechanism of action is unknown; however, it is believed ECZEMOL®addresses a primary genetic biochemical defect.

POTASSIUM BROMIDEdissolves and dissociates in the digestive tract into its ionic constituents. Each tablet contains approximately 15 mg of bromide (calculated). Ionic bromide is rapidly and completely absorbed from the intestine and distributed almost exclusively in the extracellular fluids.^7,8Bromide is eliminated by the kidneys and the elimination half-life is 11-12 days. "Once a day" dosing will lead to a steady state concentration in about seven weeks.^7

SULPHURis a naturally occurring mineral that is an essential part of the human body. It exhibits anti-bacterial, anti-parasitic, fungicidal, and keratolytic properties.^26Each tablet contains approximately 1.5 mg of sulphur (calculated). Sulphur is highly water soluble and as a result is easily excreted by the body via sweat and urine.^22Since the sulphur found in ECZEMOL®is a naturally occurring mineral, it is radically different from sulfa drugs (sulfonamide antibiotics). Therefore, patients who are allergic to sulfa drugs CAN safely take ECZEMOL®.

NICKEL SULPHATEdissolves and dissociates in the digestive tract into its ionic constituents. Each tablet contains approximately 0.5 mg of ionic nickel (calculated). According to studies, 15% to 50% of ionic nickel is absorbed on a fasted stomach.^2Food markedly decreases the rate and extent of nickel absorption.^3,4Clinical studies show that serum concentrations of nickel are variable among patients after administering the same dosage.^5Peak serum nickel concentration is reached about two hours after oral administration. "Once a day" dosing leads to steady state serum concentrations in approximately one week. Nickel is in its highly stable divalent cation state and is therefore not expected to be metabolized to any significant degree in the body. Absorbed nickel is primarily excreted in the urine and elimination half-life is about 21 hours.^3,5Renal clearance is rapid and efficient, and nickel does not accumulate in the body.^6

CLINICAL STUDIES

A variety of controlled clinical studies have been performed using various sources of both nickel and bromide in over 300 subjects. Clinical efficacy and safety have been documented in a significant number of subjects. Published and unpublished reports are available upon request.^9,20,21

INDICATIONS

ECZEMOL®is indicated for the treatment of moderate to severe eczema and atopic dermatitis. It has been found to work well with a variety of combination therapies.

CONTRAINDICATIONS

Although there are no known contraindications, patients who are allergic to any ECZEMOL®ingredient should consult a physician prior to taking the medication. (Refer to Section on Hypersensitivity)

WARNING

Do not use if imprinted seal under bottle cap is missing or broken. Do not use if pregnant or nursing. If allergic to nickel or metal objects such as jewelry or if there is a history of blistering hand eczema, see PRECAUTIONSfor hypersensitivity information. Lactose intolerant patients may have gastrointestinal difficulty. This has very rarely been reported at the doses used.

PRECAUTIONS

Carefully adjust dosage to weight when treating young children. Use cautiously in setting of kidney disease. (see Dosage and Administration) If skin rash appears or if nervous symptoms persist, recur frequently, or are unusual, discontinue use.

Hypersensitivity

Caution should be used when administering to patients with a history of contact sensitivity to nickel (common metal exposure) or if there is a history of vesicular hand eczema (dyshidrosis, pomphylox). Nickel allergy may be confirmed by a positive nickel patch test. Most patients with hand eczema, positive nickel allergy history, or a positive nickel patch test do nothave any untoward reaction to administration of ECZEMOL®. If there is a history of nickel sensitivity or dyshidrotic hand eczema, begin with a very low dose and slowly increase to a recommended starting dose over a period of 5 weeks as tolerated, thus allowing progressive GI absorption *.

*Nickel desensitization schedule:
Week | Amount of Time to Take Medication Prior to Breakfast
Week 1 | With Breakfast
Week 2 | 15 min Prior
Week 3 | 30 min Prior
Week 4 | 45 min Prior
Week 5 and thereon | 1 hour Prior

If new pruritic rashes occur or persist, discontinue ECZEMOL®and treat appropriately. Do not use if there is a history of extra-cutaneous hypersensitivity to nickel or any ingredient in ECZEMOL®.

Information for patients

Patients using ECZEMOL®should receive the following information and instructions:

1. This medication is to be used as directed by a physician.
2. It is important to take orally at the beginning of the day on an empty stomach (or any convenient time after having taken nothing but water for at least 7 hours) and to eat or drink nothing but water for at least one hour afterwards to avoid interference with absorption.

Drug interactions

There are no known drug interactions.

Carcinogenesis, mutagenesis, impairment of fertility

No studies have been done on the carcinogenesis, mutagenesis, or impairment of fertility of ECZEMOL®. No carcinogenesis or mutagenesis has been reported in multiple animal studies for oral administration of soluble nickel and bromide salts (active ingredients) even at very high doses.^10-14

Effects of soluble potassium bromide

KBr is not listed as a carcinogen by the NTP, IARC, and OSHA.^16

Effects of sulphur

Sulphur is not listed as a carcinogen by the ACGIH, IARC, NIOSH, NTP, or OSHA.^25

Effects of soluble nickel sulphate

Studies on experimental animals have never indicated that nickel, at any dose, is a carcinogen when introduced to the body orally. Furthermore, Nickel sulphate and other highly water soluble nickel salts, have never been known to induce carcinogenesis via any route of introduction including: oral, inhalation, cutaneous, IM, or IP.^10-12,15No adverse effects were noted on fertility or reproduction in a 3-generational study of albino Wistar rats fed up to 1000 ppm Ni per day, which is equivalent to 50 mg/kg body weight per day Ni.^15

Pregnancy

Pregnancy category C

Animal reproduction studies have not been conducted with ECZEMOL®. ECZEMOL®should not be given to a pregnant woman.

Nursing mothers

It is not known whether this drug is excreted in human milk. However, since many drugs are excreted in human milk, caution should be exercised when ECZEMOL®is administered to a nursing woman.

Pediatric use

Carefully adjust dosage to weight when treating young children.

ADVERSE REACTIONS

ECZEMOL®contains low doses of active ingredients. Therefore there are minimal known side effects. (see PRECAUTIONSfor hypersensitivity information)

OVERDOSAGE

Potassium bromide toxicity

Indications of toxicity due to oral overdosage of bromide may include nausea, vomiting, apathy, disturbed coordination, loss of memory, drowsiness, loss of emotional control, agitation, hallucination, tremors, depressed reflexes, stupor, and coma. Acute toxic reactions in humans have been reported at doses as low as 1000 mg.^19This level is 67 times the dose received in one tablet of ECZEMOL®.

Sulphur toxicity

The oral rat LD50for sulphur is reported to be greater than 5,000 mg/kg .^23This is more than 37,000 times the maximum dose recommended for ECZEMOL®. (see Dosage) Ingestion of toxic levels of sulphur can cause sore throat, nausea, headache, gastrointestinal irritation, and possibly unconsciousness in severe cases.^24,25Sulphur poses such a remote risk that it is placed in the lowest toxic category possible, EPA Toxicity Category IV.^23

Nickel sulphate toxicity

The oral rat LD50for nickel sulphate hexahydrate is 275 mg/kg.^17Symptoms of toxicity due to oral overdosage of nickel sulphate may include nausea, vomiting, abdominal discomfort, diarrhea, giddiness, lassitude, headaches, cough, and shortness of breath.^18The lowest observed transitory toxic effects from human ingestion of soluble nickel salts is approximately 8 mg nickel/kg body weight.^18This is 180 times the maximum dose recommended for ECZEMOL®. (See below)

DOSAGE AND ADMINISTRATION

Absorption of nickel sulphate is variable among individuals. For maximum absorption, tablets should be taken orally at the beginning of the day(or any convenient time after having taken nothing but water for at least 7 hours). Take nothing but water for one hour after taking medication to aid absorption.

Kg | lbs | Starting dose | Max Daily dose
5-11 | 11-25 | ¼ | ½
12-22 | 26-50 | ½ | 1
23-45 | 51-100 | 1 | 2
46-68 | 101-150 | 2 | 4
69-90 | 151-200 | 3 | 6
91+ | 201+ | 4 | 8

In the setting of renal impairment

Dosage should be adjusted and serum nickel and bromide levels should be followed. Steady state trough level should be drawn prior to ingesting the day's dose after one week of dosing or at appropriate intervals. Target trough serum nickel level is 20-40 mcg/L. (Caution: post dose peak levels are unreliable.) Treatment duration depends on the individual. Increase dose as needed on a monthly basis. Try b.i.d. dosing (upon rising and at bedtime) if max dose (see above) is not effective; do not exceed max daily dose.

Maintenance phase

In order to maintain symptomatic relief, medication may be continued at the same or reduced initial phase dose level.

HOW SUPPLIED

Scored tablets, off white in color with green speckles, with and scoreimprinted on same side, in child-resistant and tamper-resistant bottles of 100. NDC 61480-127-05

RxSales@PlymouthPharmaceuticals.com

www.PlymouthPharmaceuticals.com

Plymouth Pharmaceuticals Inc. dba LOMA LUX Laboratories; P.O. BOX 702418; Tulsa, OK 74170-2418

Phone 800.316.9636, 918.664.9882, Fax 918.664.9884

Revised 2.7.06 mn

PRINCIPAL DISPLAY PANEL - 100 Tablet Bottle Label

NDC 61480-127-05
Homeopathic Medication

ECZEMOL®

Indicated for treatment of
ECZEMA

100 Tablets